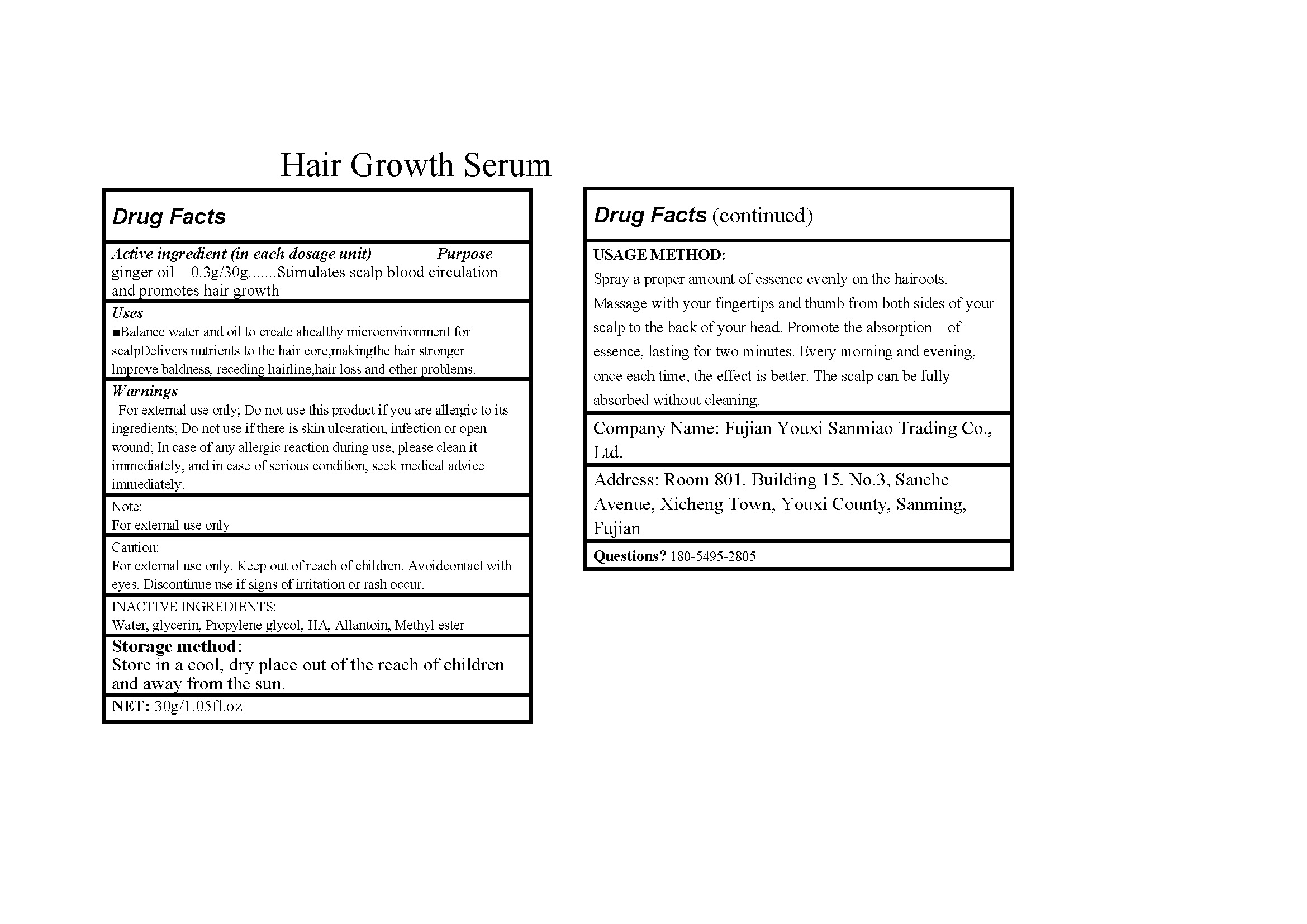 DRUG LABEL: Hair growth serum
NDC: 84518-001 | Form: LIQUID
Manufacturer: Fujian Youxi Sanmiao Trading Co., Ltd.
Category: otc | Type: HUMAN OTC DRUG LABEL
Date: 20240709

ACTIVE INGREDIENTS: GINGER OIL 0.3 g/30 g
INACTIVE INGREDIENTS: WATER; GLYCERIN; PROPYLENE GLYCOL; HYALURONATE SODIUM; ALLANTOIN; METHYLPARABEN

84518-001-11

Active ingredient: ginger oil 0.3g/30g

PURPOSE

Purpose: Stimulates scalp blood circulation and promotes hair growth

INDICATIONS AND USAGE

Uses: Balance water and oil to create ahealthy microenvironment for scalpDelivers nutrients to the hair core,makingthe hair stronger

lmprove baldness, receding hairline,hair loss and other problems.

WARNINGS

Warnings: For external use only; Do not use this product if you are allergic to its ingredients; Do not use if there is skin ulceration, infection or open wound; In case of any allergic reaction during use, please clean it immediately, and in case of serious condition, seek medical advice immediately.

KEEP OUT OF REACH OF CHILDREN

Caution: For external use only. Keep out of reach of children. Avoidcontact with eyes. Discontinue use if signs of irritation or rash occur.

INACTIVE INGREDIENT

INACTIVE INGREDIENTS: Water, glycerin, Propylene glycol, HA, Allantoin, Methyl ester

STORAGE AND HANDLING

Storage method: Store in a cool, dry place out of the reach of children and away from the sun.

DOSAGE AND ADMINISTRATION

USAGE METHOD:

Spray a proper amount of essence evenly on the hairoots. Massage with your fingertips and thumb from both sides of your scalp to the back of your head. Promote the absorption of essence, lasting for two minutes. Every morning and evening, once each time, the effect is better. The scalp can be fully absorbed without cleaning.

STATEMENT OF IDENTITY

Company Name: Fujian Youxi Sanmiao Trading Co., Ltd.

Address: Room 801, No. 3 Sanche Avenue, Xicheng Town, Youxi County, Sanming City, Fujian Province

Questions?

180-5495-2805

Label